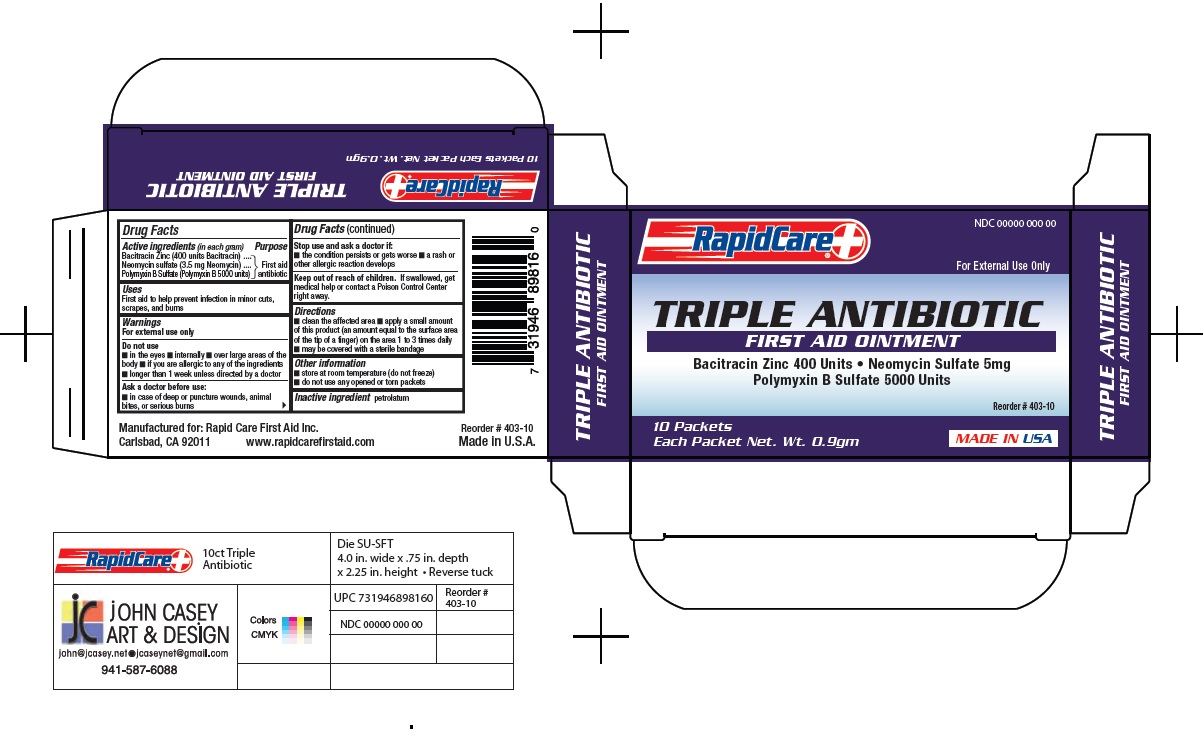 DRUG LABEL: Triple Antibiotic
NDC: 73659-005 | Form: SWAB
Manufacturer: Rapid Care, Inc
Category: otc | Type: HUMAN OTC DRUG LABEL
Date: 20201215

ACTIVE INGREDIENTS: POLYMYXIN B SULFATE 5000 [USP'U]/1 g; BACITRACIN ZINC 400 [USP'U]/1 g; NEOMYCIN SULFATE 3.5 mg/1 g
INACTIVE INGREDIENTS: PETROLATUM

RapidCare - Triple Antibiotic Towelette - 10 Packet

Active Ingredients

(in each gram)

Bacitracin zinc 400 units

Neomycin sulfate (3.5mg Neomycin)

Polymyxin B sulfate 5000 units

Purpose

Antibiotics

Use

first aid to help prevent infection in minor cuts, scrapes or burns

Warnings

For external use only

Do Not Use

- internally
- in eyes
- over large areas of the body or on puncture wounds, animal bites or serious burns
- for more than 1 week unless directed by a doctor
- if you are allergic to any of the ingredients

Stop use and ask a doctor:

- a rash or allergic reation develops
- condition worsens or persists

Keep out of reach of children.

If swallowed get medical help or contact a Poison Control right away.

Directions

- clean affected area
- apply a small amount 1 to 3 times daily
- may cover with a sterile bandage

Inactive ingredients

petrolatum